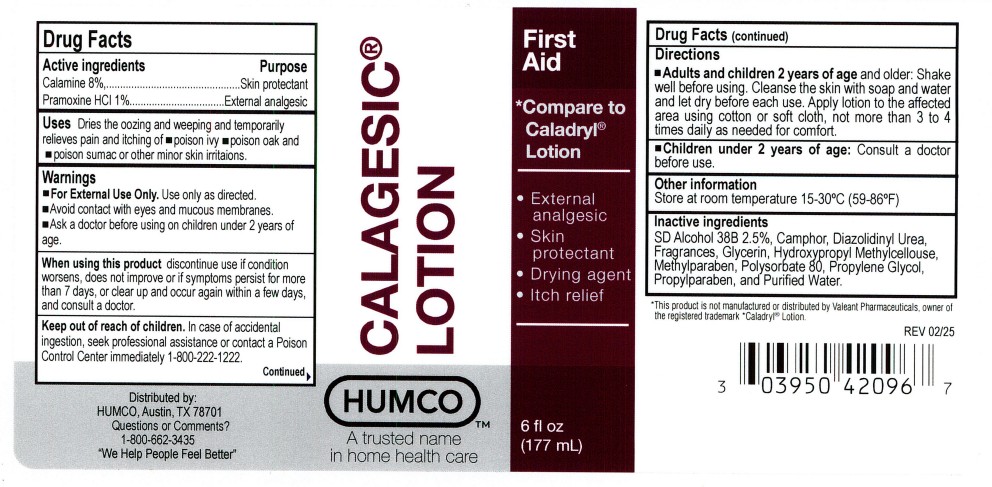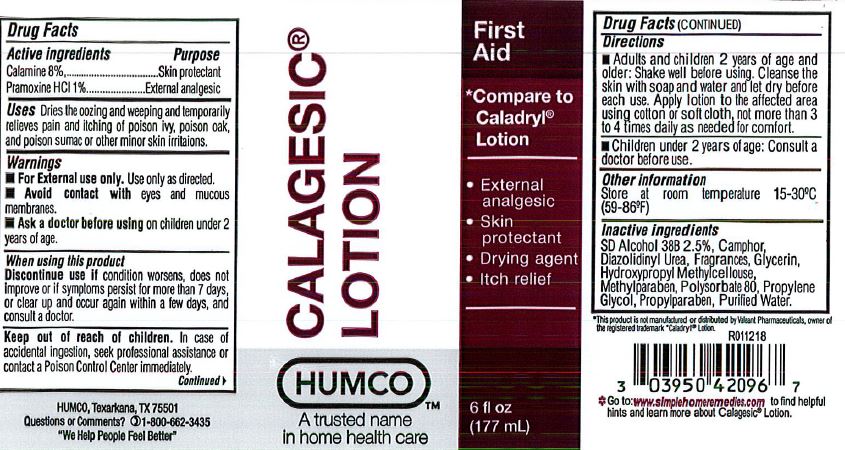 DRUG LABEL: Humco Calagesic
NDC: 0395-0420 | Form: LOTION
Manufacturer: Humco Holding Group, Inc.
Category: otc | Type: HUMAN OTC DRUG LABEL
Date: 20251211

ACTIVE INGREDIENTS: ZINC OXIDE 80 mg/1 mL; PRAMOXINE HYDROCHLORIDE 10 mg/1 mL
INACTIVE INGREDIENTS: CAMPHOR (NATURAL); DIAZOLIDINYL UREA; GLYCERIN; METHYLPARABEN; POLYSORBATE 80; PROPYLENE GLYCOL; PROPYLPARABEN; WATER

Humco Calagesic Lotion

Drug Facts

Active Ingredients

Calamine 8%

Pramoxine HCl 1%

Purpose

Skin Protectant

External analgesic

Uses

Dries the oozing and weeping, and temporarily relieves pain and itching of poison ivy, oak, and sumac or other skin irritations.

Warnings

For external use only. Use only as directed.

When using this product. Avoid contact with eyes and moucous membranes.

Stop use and ask a doctor if

condition worsens. Symptoms last for more than 7 days or clear up and occur again within a few days.

Keep out of reach of children.

In case of accidental ingestion, seek profesional assistance or contact a Poison Control Center immediately.

Directions

Adults and children 2 yr. of age and older. Shake well before using. Cleanse the skin with soap and water and let dry. Apply to the affected area using cotton or soft cloth, not more than 3 to 4 times daily as needed for comfort.

Children under 2 yrs. of age. Consult a doctor before use.

Inactive Ingredients

SD Alcohol 38B 2.5%, Camphor, Diazolidinyl Urea, Fragrances, Glycerin, Hydroxypropyl Methycelulose, Methylparaben, Polysorbate 80, Propylene Glycol, Propylparaben and Purified Water.

Other information

Store at room temperature 15-30C (59-86F)